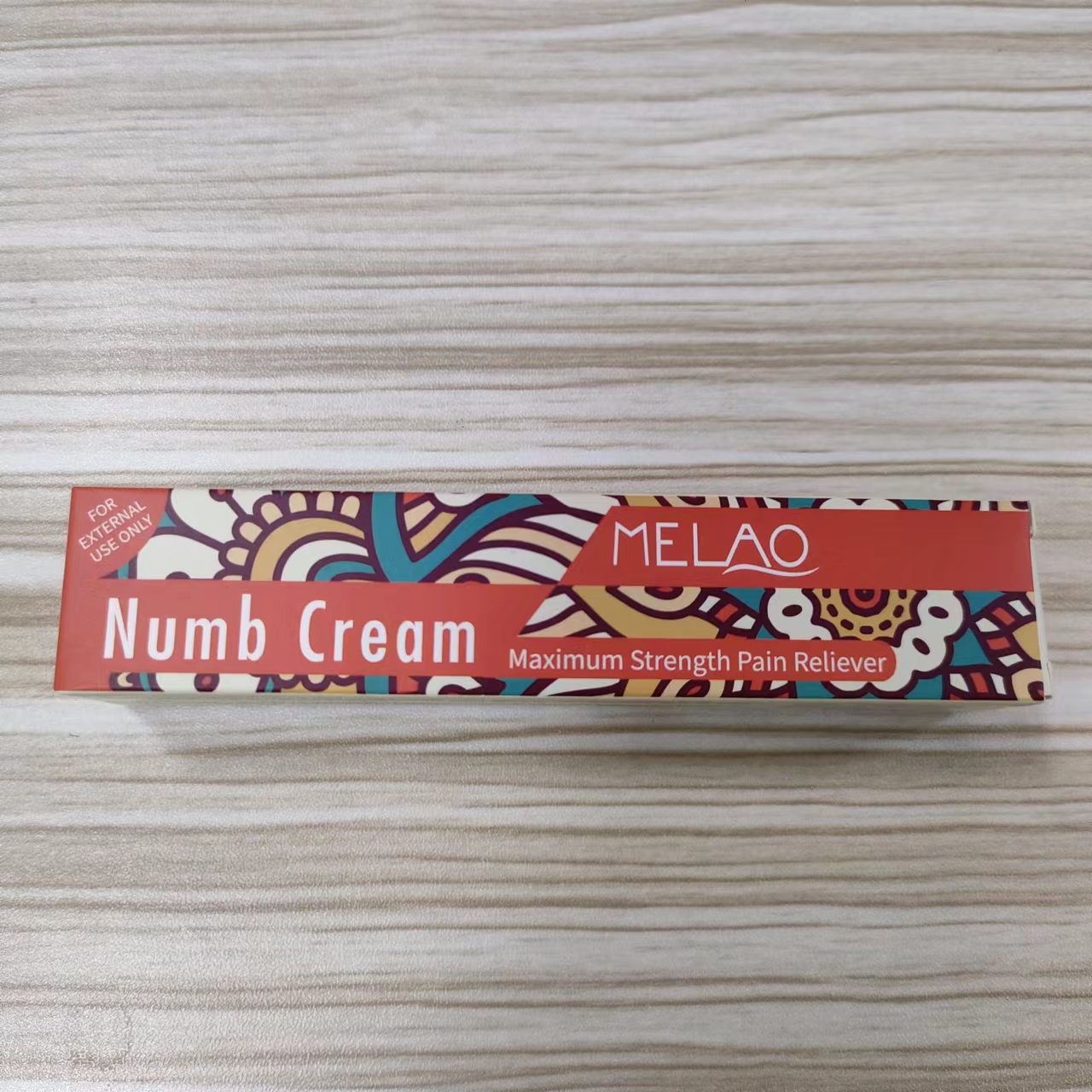 DRUG LABEL: MELAO Numb Cream
NDC: 74458-257 | Form: CREAM
Manufacturer: Guangzhou Yilong Cosmetics Co., Ltd
Category: otc | Type: HUMAN OTC DRUG LABEL
Date: 20241007

ACTIVE INGREDIENTS: LIDOCAINE 0.002 g/100 g
INACTIVE INGREDIENTS: WATER; EDETATE DISODIUM; 1,2-HEXANEDIOL; TETRACAINE; PRILOCAINE; HYDROXYACETOPHENONE; CARBOMER HOMOPOLYMER, UNSPECIFIED TYPE; PROPYLENE GLYCOL; CHRYSANTHELLUM INDICUM TOP; PURSLANE; GLYCERIN; MENTHA ARVENSIS LEAF; POLYOXYL 40 HYDROGENATED CASTOR OIL

MELAO Numb Cream

ACTIVE INGREDIENT

LIDOCAINE 0.2%

INACTIVE INGREDIENT

AQUA

PROPYLENE GLYCOL

CARBOMER

GLYCERIN

DISODIUM EDTA

HYDROXYACETOPHENONE

1.2-HEXANEDIOL

MENTHA ARVENSIS LEAF EXTRACT

CHRYSANTHELLUM INDICUM EXTRACT

PORTULACA OLERACEA EXTRACT

PEG-40 HYDROGENATED CASTOR OIL

TETRACAINE

PRILOCAINE

INDICATIONS AND USAGE

For temporary relief of local discomfort, itching, pain,soreness or burning in the perianal area associated with anorectal disorders.

WARNINGS

For external use only.

PURPOSE

Soothes and calms the skin after a tattoo.

Stop use and ask a doctor if rash occurs.

Do not use on damaged or broken skin.

When using this product keep out of eyes. Rinse with water to remove.

Keep out of reach of children. If swallowed, get medical help or contact a Poison Control Center right away.

DOSAGE AND ADMINISTRATION

For temporary relief of local discomfort, itching, pain,soreness or burning in the perianal area associated with anorectal disorders.